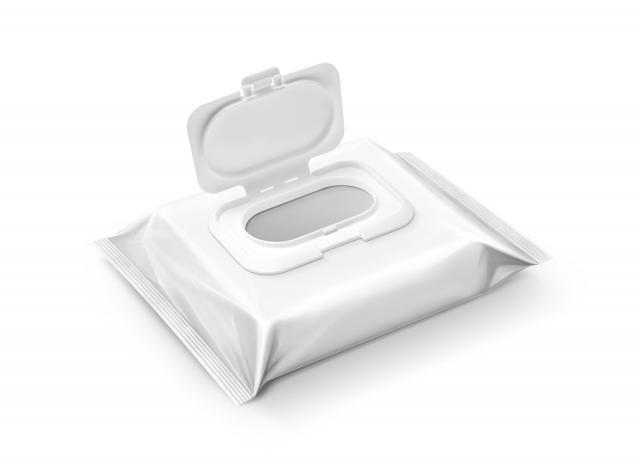 DRUG LABEL: Kenaf wet wipe kids
NDC: 72944-0004 | Form: LIQUID
Manufacturer: MEDICELL BIO CO., Ltd.
Category: otc | Type: HUMAN OTC DRUG LABEL
Date: 20250624

ACTIVE INGREDIENTS: ALLANTOIN 0.05 g/100 g
INACTIVE INGREDIENTS: WATER; 1,2-HEXANEDIOL

Drug Facts

ACTIVE INGREDIENT

Allantoin 0.5%

INACTIVE INGREDIENT

Water, etc

PURPOSE

wet tissue

keep out of reach of the children

INDICATIONS AND USAGE

Apply to skin and wipe

WARNINGS

1. For external use only.

1) Do not use over the wound and irritated skin with eczema or infections

2) Discontinue using the product if signs of irritations and/or rashes occur and seek professional medical help

2. Keep the cover closed tight after use

3. Do not put the left over contents back into the container to avoid deterioration

1) Avoid contact with eyes

2) Keep out of reach of children

3) Store in a cool and dry place, away from direct sun light

DOSAGE AND ADMINISTRATION

for external use only